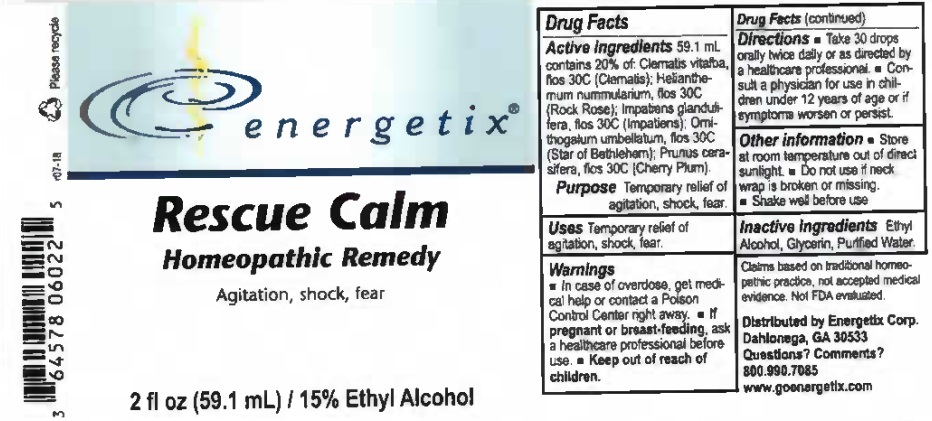 DRUG LABEL: Rescue Calm
NDC: 64578-0107 | Form: LIQUID
Manufacturer: Energetix Corp
Category: homeopathic | Type: HUMAN OTC DRUG LABEL
Date: 20181127

ACTIVE INGREDIENTS: CLEMATIS VITALBA FLOWER 30 [hp_C]/1 mL; HELIANTHEMUM NUMMULARIUM FLOWER 30 [hp_C]/1 mL; IMPATIENS GLANDULIFERA FLOWER 30 [hp_C]/1 mL; ORNITHOGALUM UMBELLATUM FLOWERING TOP 30 [hp_C]/1 mL; PRUNUS CERASIFERA FLOWER 30 [hp_C]/1 mL
INACTIVE INGREDIENTS: WATER; GLYCERIN; ALCOHOL

Drug Facts:

ACTIVE INGREDIENT

Active Ingredients59.1 mL contains 20% of: Clematis vitalba, flos 30C (Clematis); Helianthemum nummularium, flos 30C (Rock Rose); Impatiens Glandulifera, flos 30C (Impatiens); Ornithogalum Umbellatum, flos 30C (Star of Bethlehem); Prunus Cerasifera, flos 30C (Cherry Plum).

Claims based on traditional homeopathic practice, not accepted medical evidence. Not FDA evaluated.

Warnings

- In case of overdose, get medical help or contact a Poison Control Center right away.

- If pregnant or breast feeding, ask a healthcare professional before use.
- Keep out of reach of children.

- KEEP OUT OF THE REACH OF CHILDREN

Directions

- Take 30 drops orally twice daily or as directed by a healthcare professional.

- Consult a physician for use in children under 12 years of age or if symptoms worsen or persist.

Other information

- Store at room temperature out of direct sunlight.

- Do not use if neck wrap is broken or missing.

- Shake well before use.

INDICATIONS AND USAGE

Uses Temporary relief of agitation, shock, fear.

Inactive Ingredients Ethyl Alcohol, Glycerin, Purified Water

QUESTIONS

Distributed by
Energetix Corp.
Dahlonega, GA 30533

Questions? Comments?

800.990.7085
www.goenergetix.com

PACKAGE LABEL

energetix

Rescue Calm

Homeopathic Remedy

Agitation, shock, fear.

2 fl oz (59.1 mL) 15% Ethyl Alcohol

Purpose Agitation, shock, fear.